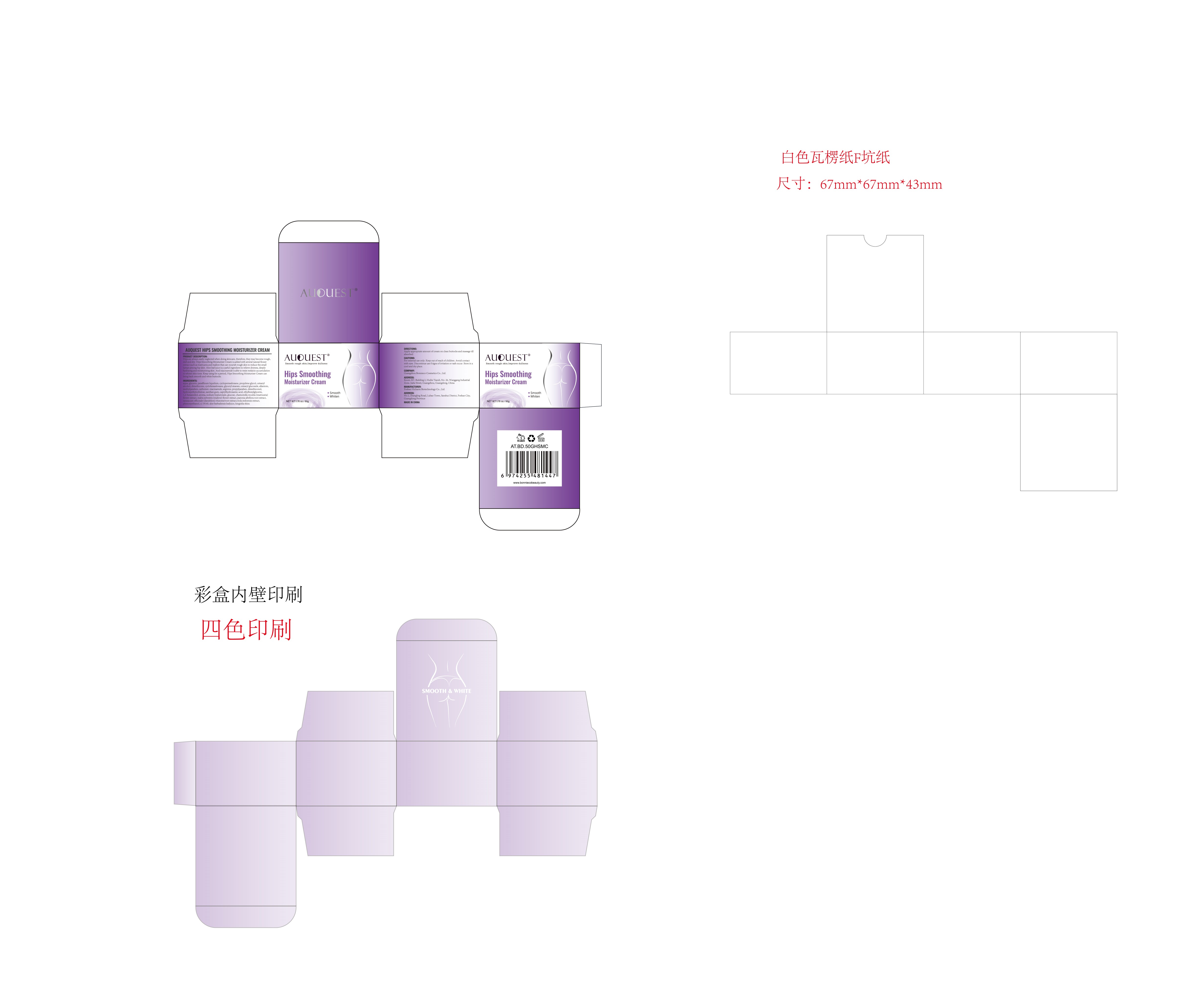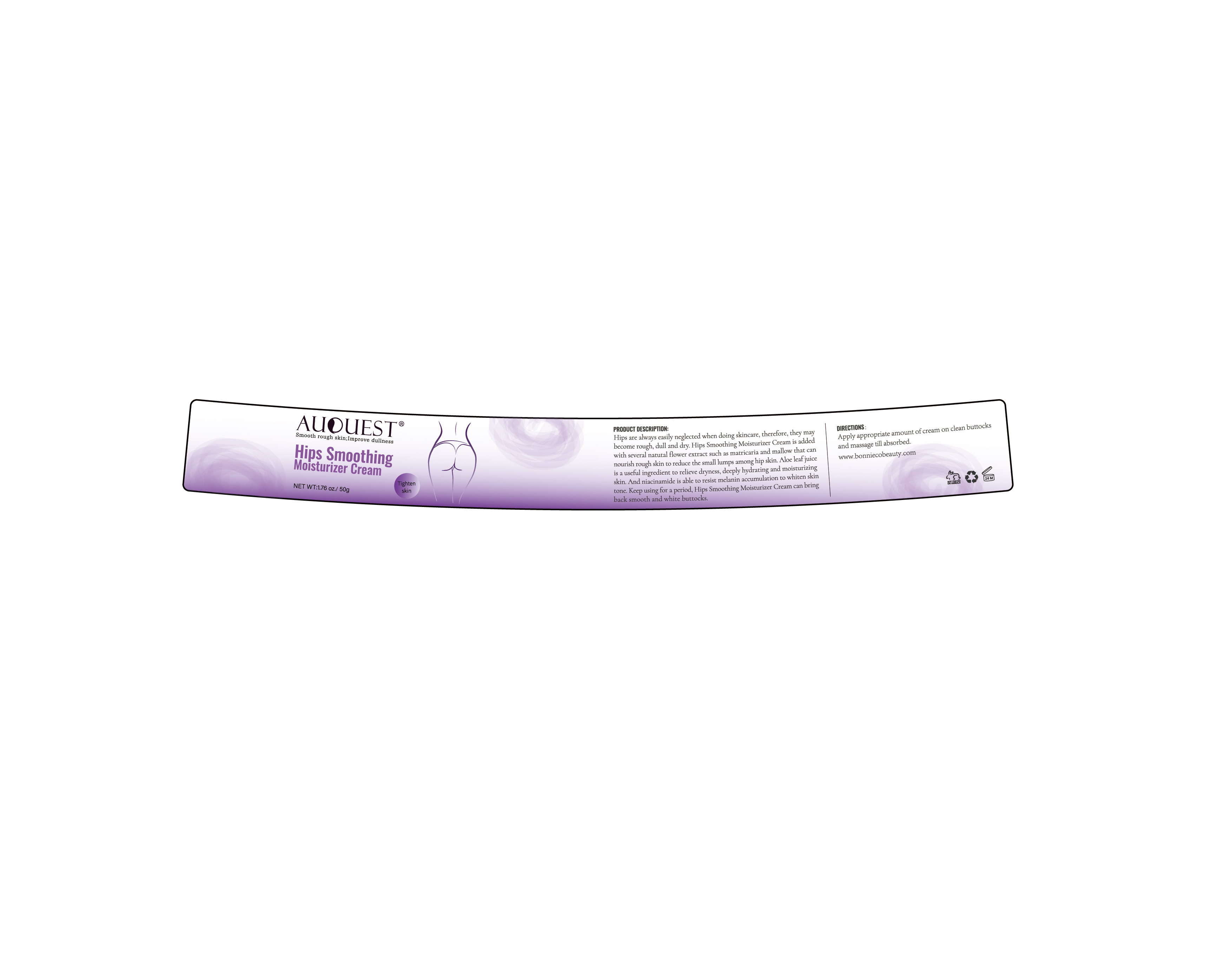 DRUG LABEL: AuQuest Hips SmoothingMoisturizer Cream
NDC: 84186-015 | Form: CREAM
Manufacturer: Guangzhou Bonnieco Cosmetics Co., Ltd
Category: otc | Type: HUMAN OTC DRUG LABEL
Date: 20240409

ACTIVE INGREDIENTS: GLYCERIN 6 g/100 g
INACTIVE INGREDIENTS: HEXANOHYDROXAMIC ACID; MALVA SYLVESTRIS FLOWER; PHENOXYETHANOL; FD&C YELLOW NO. 5; DIMETHICONE; ALLANTOIN; METHYLPARABEN; NIACINAMIDE; ARGININE; ANHYDROUS DEXTROSE; PAEONIA LACTIFLORA ROOT; VIOLA PHILIPPICA WHOLE; ALOE VERA LEAF; KING DORY; CHAMOMILE; CYCLOMETHICONE 6; CETEARYL GLUCOSIDE; ETHYLHEXYLGLYCERIN; SURFOMER; 1,2-HEXANEDIOL; TARAXACUM OFFICINALE; MINERAL OIL; PROPYLPARABEN; CYCLOMETHICONE 5; HYDROXYETHYL CELLULOSE, UNSPECIFIED; PEG-9 DIGLYCIDYL ETHER/SODIUM HYALURONATE CROSSPOLYMER; WATER; PROPYLENE GLYCOL; CETOSTEARYL ALCOHOL; GLYCERYL MONOSTEARATE; CARBOMER HOMOPOLYMER, UNSPECIFIED TYPE; XANTHAN GUM

84186-015

Active Ingredient

Glycerin 6%

Purpose

buttocks

Use

Apply appropriate amount of cream on clean buttocks and massage tillabsorbed.

Warnings

For external use only. Keep out of reach of children.Avoid contactwith eyes. Discontinue use if signs of irritation or rash occur.Store in acool and dry place.

Do not use

Hips are always easily neglected when doing skincare, therefore, they may become rough,dull and dry. Hips Smoothing Moisturizer Cream is added with several natutal flowerextract such as matricaria and mallow that can nourish rough skin to reduce the smalllumps among hip skin. Aloe leaf juice is a useful ingredient to relieve dryness, deepl，hydrating and moisturizing skin.And niacinamide is able to resist melanin accumulationto whiten skin tone.Keep using for a period, Hips Smoothing Moisturizer Cream canbring back smooth and white buttocks.

When Using

In case of contact with the eyes, rinse immediately with plenty of water.

Stop Use

If discomfort arises, please immediately stop using the product and seek the assistance of a dermatologist.

Ask Doctor

If discomfort arises, please immediately stop using the product and seek the assistance of a dermatologist.

Keep Oot Of Reach Of Children

Directions

Apply appropriate amount of cream on clean buttocks and massage tillabsorbed.

Inactive ingredients

aqua, paraffinum liquidum, cyclopentasiloxane, propylene glycol, cetearylalcohol, dimethicone, cyclohexasiloxane,glyceryl stearate, cetearyl glucoside, allantoin,methylparaben, carbomer, niacinamide, arginine, propylparaben, dimethiconol,hydroxyethylcellulose, xanthan gum, caprylhydroxamic acid, ethylhexylglycerin,1,2-hexanediol, aroma, sodium hyaluronate, glucose, chamomilla recutita (matricaria)flower extract, malva sylvestris (mallow) flower extract, paeonia albiflora root extracttaraxacum officinale (dandelion) rhizome/root extract,viola yedoensis extract,phenoxyethanol, ci 19140, aloe barbadensis leafjuice,kinginka ekisu